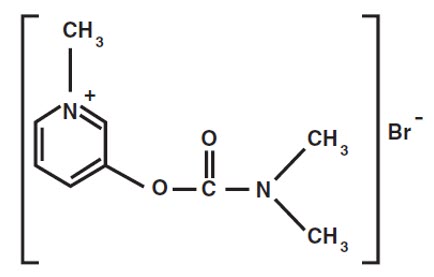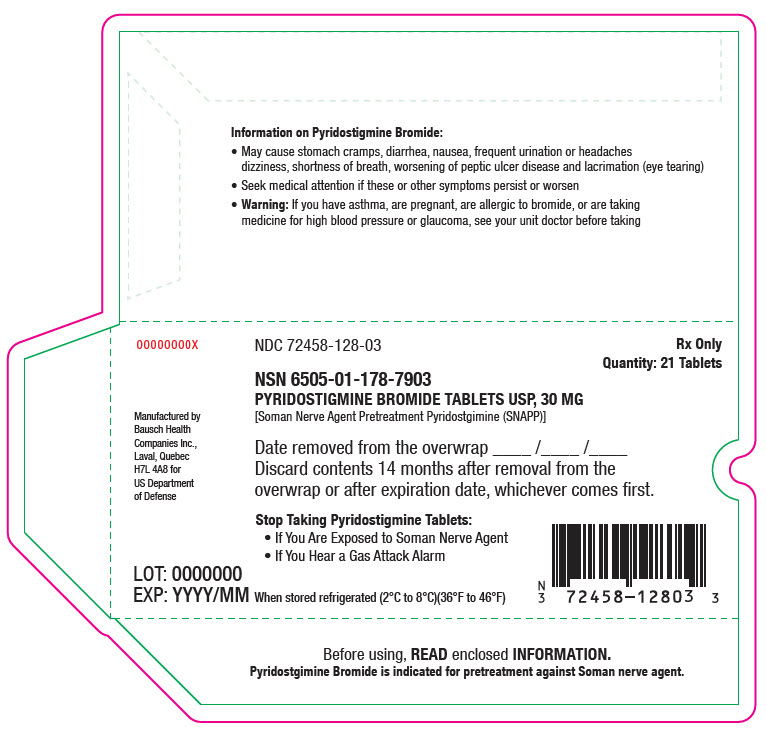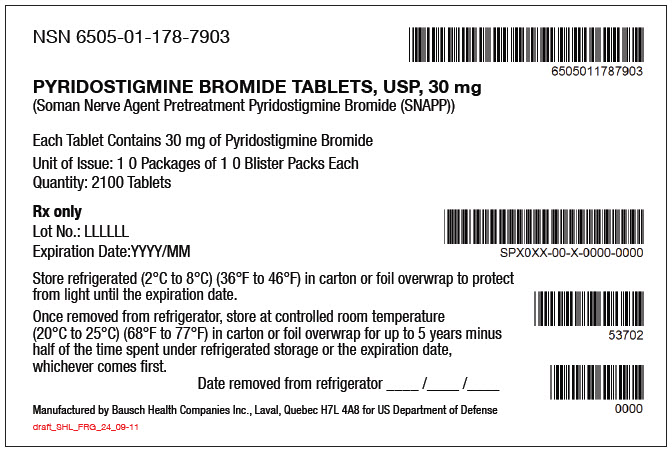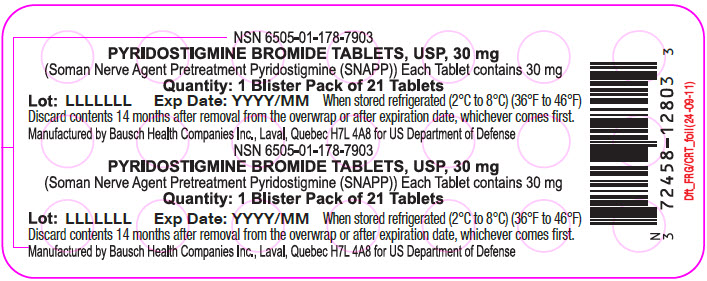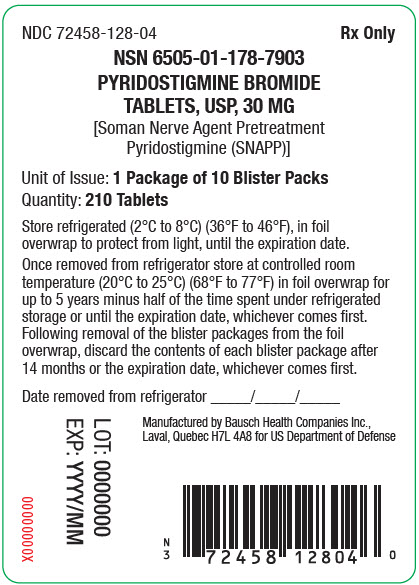 DRUG LABEL: Pyridostigmine Bromide
NDC: 72458-128 | Form: TABLET
Manufacturer: Surgeon General-Department of the Army (TSG-DA)
Category: prescription | Type: HUMAN PRESCRIPTION DRUG LABEL
Date: 20251223

ACTIVE INGREDIENTS: PYRIDOSTIGMINE BROMIDE 30 mg/1 1
INACTIVE INGREDIENTS: ANHYDROUS LACTOSE; SILICON DIOXIDE; STEARIC ACID

HIGHLIGHTS OF PRESCRIBING INFORMATION

These highlights do not include all the information needed to use PYRIDOSTIGMINE BROMIDE TABLETS safely and effectively. See full prescribing information for PYRIDOSTIGMINE BROMIDE TABLETS .
PYRIDOSTIGMINE BROMIDE tablets, for oral use
Initial U.S. Approval: 1955

WARNING: RISKS WITH IMPROPER USE OF PYRIDOSTIGMINE BROMIDE

See full prescribing information for complete boxed warning.

After Exposure to Soman, Use Atropine and Pralidoxime

- Pyridostigmine bromide is for use as a pretreatment for exposure to soman nerve agent. Pyridostigmine bromide alone will not protect against exposure to soman. The efficacy of pyridostigmine bromide is dependent upon the rapid use of atropine and pralidoxime (2-PAM) after soman exposure. (2.1, 5.1)
  Always Use Protective Garment(s)
- Primary protection against exposure to chemical nerve agents is the wearing of protective garments. (2.1, 5.1)
  Use Pyridostigmine Bromide as Pretreatment Only
- If taken immediately before soman exposure (e.g., when the gas attack alarm is given) or at the same time as poisoning by soman, it is not expected to be effective and may exacerbate the effects of a sublethal exposure to soman. Do not take pyridostigmine bromide after exposure to soman. (2.1, 12.2)

RECENT MAJOR CHANGES

Contraindications (4) | 09/2025
Warnings and Precautions (5.2) | 09/2025

1 INDICATIONS AND USAGE

Pyridostigmine bromide is a cholinesterase inhibitor indicated for pretreatment against the lethal effects of soman nerve agent poisoning in adults. (1)

Pyridostigmine bromide is for use in conjunction with:

- Protective garments, including a gas mask, and
- Immediate atropine and pralidoxime therapy at the first sign of nerve agent poisoning. (1)

2 DOSAGE AND ADMINISTRATION

- The recommended dosage is 30 mg orally every 8 hours, started at least one (1) hour prior to exposure to Soman. (2.2)
- At the first sign of soman nerve agent poisoning, discontinue pyridostigmine and administer atropine and 2-PAM. (2.2)
- Evaluate use beyond 14 consecutive days in the context of the likelihood of soman exposure. (2.2)

3 DOSAGE FORMS AND STRENGTHS

Tablets: 30 mg of pyridostigmine bromide (3)

4 CONTRAINDICATIONS

- Mechanical intestinal or urinary obstruction. (4)
- Known hypersensitivity to pyridostigmine or other anticholinesterase agents. (4)

5 WARNINGS AND PRECAUTIONS

- At the first sign of soman poisoning, pyridostigmine must be stopped, and atropine and 2-PAM must be administered immediately. (5.1)
- Use with caution in persons with increased risk of anticholinergic reactions, such as persons with bronchial asthma, chronic obstructive pulmonary disease, bradycardia, cardiac arrhythmias, beta blocker treatment (increased risk of anticholinergic reactions). (5.2)
- Use with caution in persons with bromide sensitivity. (5.3)
- In case of serious adverse reactions, advise personnel to temporarily discontinue pyridostigmine and seek immediate medical attention. (5.4)

6 ADVERSE REACTIONS

Most common adverse reactions (≥ 3%) are diarrhea, abdominal pain, dysmenorrhea, and twitch. (6)

To report SUSPECTED ADVERSE REACTIONS, contact U.S. Army Medical Research and Development Activity at 301-619-0317 (fax 301-619-0197) or FDA at 1-800-FDA-1088 or www.fda.gov/medwatch.

7 DRUG INTERACTIONS

- Mefloquine: Additive effect on gastrointestinal tract and atrial rate. (7.1)
- Anticholinesterase drugs for glaucoma treatment: Additive effects. (7.2)
- Narcotics: Exacerbation of bradycardia possible. (7.3)
- Depolarizing neuromuscular blocking agents: Increased effect. (7.4)
- Non-depolarizing neuromuscular blocking agents: Dose may need to be increased. (7.4)
- Aminoglycoside antibiotics, local and some general anesthetics, anti-arrhythmic agents, and other drugs that interfere with neuromuscular transmission should be used cautiously, if at all. (7.4)
- Drugs converted to pantothenic acid (e.g., dexpanthenol): Additive effect. (7.5)

8 USE IN SPECIFIC POPULATIONS

Renal impairment: Increased risk of side effects; careful dose selection. In persons with renal impairment, renal function monitoring may be useful. (8.6)

FULL PRESCRIBING INFORMATION

WARNING: RISKS WITH IMPROPER USE OF PYRIDOSTIGMINE BROMIDE

After Exposure to Soman, Use Atropine and Pralidoxime

- Pyridostigmine bromide is for use as a pretreatment for exposure to soman nerve agent. Pyridostigmine bromide alone will not protect against exposure to soman. The efficacy of pyridostigmine bromide is dependent upon the rapid use of atropine and pralidoxime (2-PAM) after soman exposure [see Dosage and Administration (2.1) and Warnings and Precautions (5.1)].

Always Use Protective Garment(s)

- Primary protection against exposure to chemical nerve agents is the wearing of protective garments including masks, hoods, and overgarments designed specifically for this use.
- Individuals must not rely solely upon pretreatment with pyridostigmine bromide and on the antidotes atropine and pralidoxime (2-PAM) to provide complete protection from poisoning by soman nerve agent [see Dosage and Administration (2.1)].

Pyridostigmine Bromide as Pretreatment Only

- If pyridostigmine bromide is taken immediately before exposure (e.g., when the gas attack alarm is given) or at the same time as poisoning by soman, it is not expected to be effective and may exacerbate the effects of a sublethal exposure to soman. Do not take pyridostigmine bromide after exposure to soman.[see Clinical Pharmacology (12.2)].

FOR MILITARY MEDICAL USE ONLY

1 INDICATIONS AND USAGE

Pyridostigmine bromide is indicated for pretreatment against the lethal effects of soman nerve agent poisoning in adults. Pyridostigmine bromide is intended for use in conjunction with protective garments, including a mask. At the first sign of nerve agent poisoning, pyridostigmine bromide should be stopped, and atropine and pralidoxime therapy started immediately.

The evidence for the effectiveness of pyridostigmine bromide as pretreatment against soman-induced toxicity was derived from animal studies alone [see Clinical Studies (14)].

FOR MILITARY MEDICAL USE ONLY

2 DOSAGE AND ADMINISTRATION

2.1 Important Administration Information

For Military Medical Use Only.

Treatment and Protection for Soman Exposure

Pyridostigmine bromide is for use as a pretreatment for exposure to soman nerve agent (see Treatment Timing). Pyridostigmine bromide alone will not protect against exposure to soman.

Atropine and Pralidoxime

The efficacy of pyridostigmine bromide is dependent upon the rapid use of atropine and pralidoxime (2-PAM) after soman exposure.

Primary Protection

The primary protection against exposure to chemical nerve agents consists of wearing protective garments including masks, hoods, and overgarments designed specifically for this use.

Do not rely solely upon pretreatment with pyridostigmine bromide and the antidotes atropine and pralidoxime to provide complete protection from poisoning by soman nerve agent.

Treatment Timing

Pyridostigmine bromide is to be administered as pretreatment before exposure to soman nerve agent [see Dosage and Administration (2.2)]. If pyridostigmine bromide is taken immediately before exposure (e.g., when the gas attack alarm is given) or at the same time as poisoning by soman, it is not expected to be effective and may exacerbate the effects of a sublethal exposure to soman [see Clinical Pharmacology (12.2)]. Do not take pyridostigmine bromide after exposure to soman.

2.2 Recommended Dosage, Administration, and Duration

Dosage

The recommended dosage of pyridostigmine bromide is one 30-mg tablet by mouth every 8 hours, started at least several hours prior to exposure to soman.

Timing and Duration of Treatment

Timing

Pyridostigmine is a pretreatment for exposure to soman nerve agent. There is no known advantage to taking pyridostigmine bromide just prior to or concurrent with soman exposure. According to the mechanism of action of pyridostigmine bromide [see Clinical Pharmacology (12.1, 12.2)], pyridostigmine bromide is effective when it is given sufficiently in advance of soman poisoning to provide a pool of protected enzyme. Therefore, it is expected that pyridostigmine bromide will not be effective if administered just prior to or during exposure to soman.

Duration

At the first sign of nerve agent poisoning, discontinue pyridostigmine bromide and administer pretreatment with atropine and pralidoxime immediately [see Warnings and Precautions (5.1)].

The benefits and risks of use beyond 14 consecutive days have not been definitively established; therefore, evaluate continued use beyond 14 consecutive days in the context of the likelihood of exposure to soman nerve agent.

Missed Dose

If a dose is missed, take the missed dose as soon as possible. Do not take double or extra doses.

3 DOSAGE FORMS AND STRENGTHS

Tablets: 30 mg of pyridostigmine bromide, round, white and imprinted with the letters "PBT"

4 CONTRAINDICATIONS

Pyridostigmine bromide is contraindicated in patients with:

- Mechanical intestinal or urinary obstruction
- Known hypersensitivity to pyridostigmine or other anticholinesterase agents

5 WARNINGS AND PRECAUTIONS

5.1 Risk of Improper Use of Pyridostigmine Bromide

Risk of Not Stopping Pyridostigmine Bromide and Using Atropine and Pralidoxime in the Event of Soman Exposure

Pyridostigmine bromide is for use as pretreatment for exposure to soman nerve agent and must not be taken after exposure to soman nerve agent [see Dosage and Administration (2.1, 2.2)]. Pyridostigmine bromide pretreatment offers no benefit against the nerve agent soman unless the nerve agent antidotes, atropine and pralidoxime (2-PAM), are administered once symptoms of poisoning appear.

Discontinue pyridostigmine at the first sign of nerve agent poisoning because it may exacerbate the effects of a sublethal exposure to soman if taken immediately before exposure (e.g., when the gas attack alarm is given) or at the same time as poisoning by soman [see Clinical Pharmacology (12.2)]. Signs of nerve agent poisoning can include runny nose; watery eyes; small, pinpoint pupils; eye pain; blurred vision; drooling and excessive sweating; cough; chest tightness; rapid breathing; diarrhea; increased urination; confusion; drowsiness; weakness; headache; nausea, vomiting, and/or abdominal pain; slow or fast heart rate; and/or abnormally low or high blood pressure.

Risk of Not Wearing Protective Garments

Pyridostigmine bromide is not the primary protection against exposure to soman nerve agent.

The primary protection against exposure to chemical nerve agents is the wearing of protective garments including masks, hoods, and overgarments designed specifically for this use. Individuals must not rely solely upon pretreatment with pyridostigmine bromide and on the antidotes, atropine and pralidoxime (2-PAM), to provide complete protection from poisoning by soman nerve agent.

5.2 Increased Risk of Anticholinergic Adverse Reactions in Individuals with Certain Conditions

Pulmonary Conditions

Drugs that increase cholinergic activity, including pyridostigmine bromide, should be used with caution in persons with bronchial asthma or chronic obstructive pulmonary disease.

Cardiovascular Conditions

Because pyridostigmine bromide increases cholinergic activity, it may have vagotonic effects on heart rate, which can lead to bradycardia or cardiac arrhythmias.

Genitourinary Tract or Gastrointestinal Tract Obstruction

Drugs that increase cholinergic agents, including pyridostigmine bromide, could cause symptoms in persons susceptible to genitourinary tract or gastrointestinal tract obstruction.

Conditions Treated with Beta Adrenergic Receptor Blockers

Pyridostigmine bromide should be used with caution in people being treated for hypertension or glaucoma with beta adrenergic receptor blockers [see Drug Interactions (7.2)].

5.3 Use in Bromide-Sensitive Individuals

Caution should be taken when administering pyridostigmine bromide to individuals with known bromide sensitivity. As with any compound containing bromide, a skin rash may be observed in bromide-sensitive patients, which usually subsides promptly upon discontinuance of the medication.

The risks and benefits of administration must be weighed against the potential for rash or other adverse reactions in these individuals.

5.4 Serious Adverse Reactions, Such as Difficulty Breathing, Severe Dizziness, Loss of Consciousness

Pyridostigmine bromide can cause serious adverse reactions such as difficulty breathing, severe dizziness, or loss of consciousness. If these adverse reactions occur, patients should temporarily discontinue use of pyridostigmine bromide and seek immediate medical attention. Personnel should report serious adverse events to their commander and responsible medical officer.

6 ADVERSE REACTIONS

The following serious adverse reactions are discussed elsewhere in the labeling:

- Risk of Improper Use of Pyridostigmine Bromide [see Warnings and Precautions (5.1)]
- Individuals at Increased Risk of Anticholinergic Adverse Reactions [see Warnings and Precautions (5.2)]
- Use in Bromide-Sensitive Individuals [see Warnings and Precautions (5.3)]
- Serious Adverse Reactions, Such as Difficulty Breathing, Severe Dizziness, Loss of Consciousness [see Warnings and Precautions (5.4)]

6.1 Clinical Trials Experience

Because clinical trials are conducted under widely varying conditions, adverse reaction rates observed in the clinical trials of a drug cannot be directly compared to rates in the clinical trials of another drug and may not reflect the rates observed in practice.

The adverse reactions to pyridostigmine bromide are typically of two varieties: muscarinic and nicotinic. Muscarinic adverse reactions include abdominal cramps, bloating, flatulence, diarrhea, emesis, increased peristalsis, nausea, hypersalivation, urinary incontinence, increased bronchial secretion, diaphoresis, miosis, and lacrimation. Nicotinic adverse reactions are comprised chiefly of muscle cramps, fasciculations, and weakness.

In a controlled study of 90 healthy volunteers comparing pyridostigmine bromide 30 mg every 8 hours to placebo for 21 days, the adverse reactions that were reported in 2% or more of subjects is included in Table 1. The most common adverse reactions (≥ 3%) are diarrhea, abdominal pain, dysmenorrhea, and twitch.

Table 1: Incidence of Adverse Reactions ≥ 2%
Adverse Reaction | Pyridostigmine N = 60 % | Placebo N = 30 %
Diarrhea | 7 | 0
Abdominal pain | 7 | 0
Dysmenorrhea | 5 | 0
Twitch | 3 | 0
Myalgia | 2 | 0
Dry skin | 2 | 0
Urinary frequency | 2 | 0
Epistaxis | 2 | 0
Amblyopia | 2 | 0
Hypesthesia | 2 | 0
Neck pain | 2 | 0

Other less common adverse reactions seen during controlled and uncontrolled clinical trials for pyridostigmine include the following:

- Pulmonary: Exacerbation of acute bronchitis and asthma
- Cardiovascular: Elevated blood pressure, decreased heart rate (4-6 beats per minute), chest tightness
- Eyes: Change in vision, eye pain
- Neurologic: Headache, hypertonia, difficulty in concentrating, confusion, disturbed sleep, tingling of extremities, numbness of the tongue
- Skin: Increased sweating, rash, alopecia
- Digestive: Vomiting, borborygmi, nausea, bloating, flatulence
- General: Warm sensation, lethargy/drowsiness, depressed mood

During safety studies at the recommended dosage, there were two reports of loss of consciousness, one of which was suggestive of a seizure event as it also included urinary and fecal incontinence, stiffness of the upper torso and arms, post-syncopal skin pallor, post-syncopal confusion, and post-syncopal weakness.

Central Nervous System Adverse Reactions

Pyridostigmine bromide is a quaternary ammonium compound and does not readily cross the blood-brain barrier. Compared to the peripheral effects of pyridostigmine bromide, central nervous system (CNS) manifestations are less frequent and less serious, primarily consisting of headache and vertigo, with minor and clinically insignificant changes in heart rate, blood pressure, and respiratory function.

7 DRUG INTERACTIONS

7.1 Mefloquine

Concomitant use of mefloquine and pyridostigmine bromide may have additive effects on the gastrointestinal tract, the most common of which is loose bowels. Additive effects on the atrial rate may also occur with concomitant use of mefloquine and pyridostigmine bromide.

7.2 Other Anticholinesterase Drugs

Concomitant use of anticholinesterase drugs used in the treatment of glaucoma and pyridostigmine bromide may have an additive effect that may cause or exacerbate problems with night vision.

7.3 Narcotics

The bradycardia associated with the use of narcotics may exacerbate pyridostigmine-induced bradycardia.

7.4 Drugs that Interfere with Neuromuscular Transmission

Particular caution should be observed in the administration of depolarizing neuromuscular blocking agents (e.g., succinylcholine) during surgery since the degree of neuromuscular blockade that ensues may be enhanced by previously administered pyridostigmine bromide. Doses of nondepolarizing neuromuscular blocking agents (e.g., pancuronium bromide) may need to be increased in patients previously administered pyridostigmine bromide. Atropine antagonizes the muscarinic effects of pyridostigmine bromide, and this interaction is utilized to counteract the muscarinic symptoms of pyridostigmine bromide toxicity. Anticholinesterase agents are sometimes effective in reversing neuromuscular block induced by aminoglycoside antibiotics. However, aminoglycoside antibiotics, local and some general anesthetics, antiarrhythmic agents, and other drugs that interfere with neuromuscular transmission should be used cautiously, if at all, during treatment with pyridostigmine bromide.

7.5 Drugs Converted to Pantothenic Acid

Concomitant use of drugs that are converted to pantothenic acid in vivo (e.g., dexpanthenol) and pyridostigmine bromide may have additive effects by increasing production of acetylcholine.

8 USE IN SPECIFIC POPULATIONS

8.1 Pregnancy

Risk Summary

Available data from case reports and case series over decades of use with pyridostigmine bromide have not identified a drug-associated risk of major birth defects, miscarriage, or other adverse maternal or fetal outcomes. Treatment with pyridostigmine bromide for soman nerve agent poisoning during pregnancy should not be delayed because exposure to soman during pregnancy may increase the risk of maternal and fetal morbidity and mortality.

In animal studies, oral administration of pyridostigmine during organogenesis resulted in adverse developmental effects (increased embryofetal mortality and fetal structural abnormalities) at clinically relevant doses (see Data).

The background risk for major birth defects and miscarriage for the indicated population is unknown. All pregnancies have a background risk of birth defect, loss, or other adverse outcomes. In the U.S. general population, the estimated background risk of major birth defects and miscarriage in clinically recognized pregnancies is 2% to 4% and 15% to 20%, respectively.

Data

Animal Data

Oral administration of pyridostigmine to pregnant rats during organogenesis resulted in increases in embryofetal deaths and incidences of fetal skeletal variations at the highest dose tested (30 mg/kg/day), which was also maternally toxic. A slight increase in the incidence of hydronephrosis was observed at all dose levels (lowest dose tested was 3 mg/kg/day). A no-effect dose for adverse effects on embryofetal development in the rat was not identified. The lowest dose tested (3 mg/kg/day) is less than the recommended human dose (105 mg) on a body surface area (mg/m^2) basis.

Oral administration of pyridostigmine to pregnant rabbits during organogenesis resulted in an increase in the incidence of visceral variations at the highest dose tested (45 mg/kg/day), which was also maternally toxic. An increased incidence of blood vessel variations was observed at all doses (lowest dose tested was 5 mg/kg/day). A no-effect dose for adverse effects on embryofetal development in the rabbit was not identified. The lowest dose tested (5 mg/kg/day) is less than the recommended human dose on a body surface area (mg/m^2) basis.

8.2 Lactation

Risk Summary

Pyridostigmine bromide is present in human milk. Based on limited data, pyridostigmine bromide was not detected in the plasma of infants who were breastfed by mothers taking pyridostigmine bromide. There are no data on the effects on milk production. The developmental and health benefits of breastfeeding should be considered along with the mother's clinical need for pyridostigmine bromide and any potential adverse effects on the breastfed infant from pyridostigmine bromide or from the underlying maternal condition.

8.4 Pediatric Use

Safety and effectiveness in pediatric patients have not been established.

8.5 Geriatric Use

Clinical studies of pyridostigmine bromide did not contain sufficient numbers of subjects aged 65 and over to determine whether they respond differently than younger subjects. In general, dose selection for an elderly patient should be cautious, reflecting the greater frequency of decreased hepatic, renal, or cardiac function, and of concomitant disease or other drug therapy.

This drug is known to be substantially excreted by the kidney, and the risk of toxic reactions to this drug may be greater in patients with impaired renal function. Because elderly patients are more likely to have decreased renal function [see Clinical Pharmacology (12.3)], care should be taken in dose selection, and it may be useful to monitor renal function.

8.6 Renal Impairment

This drug is known to be substantially excreted by the kidney, and the risk of toxic reactions to this drug may be greater in patients with impaired renal function. Caution should be observed, and dosage be selected carefully, when administering pyridostigmine bromide to patients with impaired renal function [see Clinical Pharmacology (12.3)]. It may be useful to monitor renal function.

10 OVERDOSAGE

Overdosage of pyridostigmine bromide may result in cholinergic crisis, a state characterized by increasing muscle weakness that, through involvement of the muscles of respiration, may lead to death. Overdosage with pyridostigmine bromide must be differentiated from the acute manifestations of nerve agent poisoning, which may also be characterized by a cholinergic crisis.

Extremely high doses of pyridostigmine bromide may also produce CNS symptoms of agitation, restlessness, confusion, visual hallucinations, and paranoid delusions. Electrolyte abnormalities, possibly resulting from high serum bromide concentrations, also have been reported. Death may result from cardiac arrest or respiratory paralysis and pulmonary edema.

In the treatment of pyridostigmine bromide overdosage, maintaining adequate respiration is of primary importance. Tracheostomy, bronchial aspiration, and postural drainage may be required to maintain an adequate airway; respiration can be assisted mechanically if required. Supplemental oxygen may be necessary. Pyridostigmine bromide should be discontinued immediately and 1 mg to 4 mg of atropine sulfate administered intravenously. Additional doses of atropine may be given every 5 to 30 minutes as needed to control muscarinic symptoms. Atropine overdosage should be avoided, as tenacious secretions and bronchial plugs may result. It should be kept in mind that unlike muscarinic effects, the skeletal muscle effects and consequent respiratory paralysis (nicotinic effects) which can occur following pyridostigmine overdosage, are not alleviated by atropine.

11 DESCRIPTION

Pyridostigmine bromide is an orally active, reversible cholinesterase inhibitor. Pyridostigmine bromide is a white or almost white, crystalline, deliquescent powder, very soluble in water and alcohol, and practically insoluble in ether.

CAS registration number is 101-26-8.

Pyridostigmine bromide has a molecular formula of C9H13BrN2O2, with a molecular weight of 261.12. Its chemical name is: 3-hydroxy-1-methylpyridinium bromide dimethylcarbamate, and its structural formula is:

Pyridostigmine bromide tablets, USP contain 30 mg of pyridostigmine bromide (equivalent to 20.8 mg of pyridostigmine base) for oral administration. The inactive ingredients included in the tablet formula are colloidal silicon dioxide, lactose anhydrous, and stearic acid or, alternatively; lactose, magnesium stearate, silica precipitated, starch, and talc.

12 CLINICAL PHARMACOLOGY

12.1 Mechanism of Action

Pyridostigmine is a reversible cholinesterase inhibitor.

12.2 Pharmacodynamics

The mechanism of soman-induced death is reasonably well understood. Death is believed to result primarily from respiratory failure due to irreversible inhibition of the enzyme acetylcholinesterase and the consequent increase in the level of the neurotransmitter acetylcholine 1) at nicotinic receptors at the neuromuscular junction, resulting in pathological stimulation and ultimate failure of the muscles of respiration, 2) at muscarinic receptors in secretory glands and smooth muscle, resulting in excessive respiratory secretions and bronchoconstriction, and 3) at cholinergic receptors in the brain, resulting in central respiratory depression.

The effect of pyridostigmine is presumed to result from its reversible inhibition of a critical number of acetylcholinesterase active sites in the peripheral nervous system, protecting them from irreversible inhibition by soman. (Pyridostigmine bromide is not thought to enter the brain in significant amounts.) When the pyridostigmine bromide-induced inhibition of the enzyme is subsequently reversed, there is a small residual amount of enzyme activity that is adequate to sustain life (provided atropine and 2-PAM are subsequently administered). An implication of this presumed mechanism is that it is not helpful to give pyridostigmine bromide either just before or during exposure to soman [see Dosage and Administration (2.1, 2.2)].

12.3 Pharmacokinetics

Absorption

Pyridostigmine bromide is poorly absorbed from the gastrointestinal tract with an absolute bioavailability of 10% to 20%. Following a single oral dose of 30 mg pyridostigmine bromide in the fasting state, the Tmax was 2.2 ± 1.0 hours. The pharmacokinetics of pyridostigmine bromide is linear over the dose range of 30 mg to 60 mg. Following multiple doses of pyridostigmine bromide (30 mg every 8 hours for 21 days), the average steady-state trough concentration of pyridostigmine bromide was about ¼ of the peak concentration after a single dose.

Distribution

The volume of distribution was about 19 ± 12 liters, indicating that pyridostigmine bromide distributes into tissues. No information on protein binding of pyridostigmine bromide is available.

Elimination

Metabolism

Pyridostigmine bromide undergoes hydrolysis by cholinesterases and is metabolized in the liver.

Excretion

Pyridostigmine bromide is excreted in the urine as both unchanged drug and its metabolites. The systemic clearance of pyridostigmine bromide is 830 mL/min and the elimination half-life of pyridostigmine bromide is approximately 3 hours.

Specific Populations

Patients with Renal Impairment: In anephric patients (n = 4), the elimination half-life increased 3-fold and the systemic clearance decreased by 75% [see Use in Specific Populations (8.6)].

Patients with Hepatic Impairment: No information is available on the pharmacokinetics of pyridostigmine bromide in hepatic impaired patients.

Male and Female Patients: The clearance of pyridostigmine bromide is not influenced by sex.

Geriatric Patients: In a pyridostigmine bromide study in elderly subjects (71 to 85 years of age), the elimination half-life and volume of distribution (central and steady-state) of pyridostigmine were comparable with younger subjects (21 to 51 years of age). However, the systemic plasma clearance was 30% lower in the elderly compared to younger subjects (6.7 ± 2.2 vs. 9.5 ± 2.7 mL/min/kg) [see Use in Specific Populations (8.5)].

13 NONCLINICAL TOXICOLOGY

13.1 Carcinogenesis, Mutagenesis, Impairment of Fertility

Carcinogenicity

Studies to evaluate the carcinogenic potential of pyridostigmine bromide have not been conducted.

Mutagenicity

Pyridostigmine bromide was negative in in vitro (bacterial reverse mutation, mammalian gene mutation in Chinese hamster ovary (CHO) cells, clastogenicity in CHO cells) and in vivo (mouse micronucleus) assays. Pyridostigmine bromide was mutagenic and clastogenic in an in vitro mammalian gene mutation assay in mouse lymphoma cells, in the presence of metabolic activation.

Impairment of Fertility

Pyridostigmine bromide did not impair fertility in male or female rats given oral doses of up to 45 mg/kg/day (5 times the recommended human daily dose of 90 mg on a mg/m^2 basis) beginning at 10 (males) or 2 (females) weeks prior to mating.

14 CLINICAL STUDIES

The effectiveness of pyridostigmine bromide as a pretreatment against the lethal effects of soman nerve agent poisoning has not been determined in humans because adequate and well-controlled field trials have not been feasible and inducing soman nerve agent poisoning in humans to study the drug's efficacy is not ethical. Therefore, the effectiveness of pyridostigmine bromide as a pretreatment against the lethal effects of soman nerve agent poisoning was established based on the results of the following adequate and well-controlled animal efficacy studies.

While the results of these animal studies cannot be extrapolated to humans with certainty, the extrapolation is supported by the reasonably well understood pathophysiologic mechanisms of the toxicity of soman and the mechanism of the protective effect of pyridostigmine bromide pretreatment, as examined in various animal species. In addition, the results of these animal studies establish that pyridostigmine bromide is reasonably likely to produce clinical benefit in humans. The section below explains the current understanding of the mechanism of soman toxicity and the beneficial effect of pyridostigmine bromide pretreatment, as well as the basis for extrapolating the animal findings to humans.

Pyridostigmine bromide pretreatment has been shown in animals to decrease the lethality of the soman nerve agent, provided atropine and pralidoxime (2-PAM) are administered immediately after exposure to soman.

Rhesus monkeys were given oral doses of pyridostigmine bromide every 8 hours for a total of 6 doses and were challenged with soman given intramuscularly 5 hours after the last pyridostigmine bromide dose. Two dosage groups of pyridostigmine bromide were used: a low-dose group given 1.2 mg/kg for all 6 doses and a high-dose group given 1.2 and 1.8 mg/kg for the first and second doses, respectively, and 2.4 mg/kg for the final 4 doses. These animals were also given atropine and 2-PAM after exposure to soman. An untreated control group and a group given atropine and 2-PAM (but not pyridostigmine bromide) were also used. The primary endpoint in this study was a decrease in the lethality of soman expressed as an increase in the LD50 (the dose of soman that killed 50 % of the animals). The atropine/2-PAM control group showed a small but statistically significant 1.6-fold increase in the soman LD50 compared to the untreated control group. The groups given pyridostigmine bromide as well as atropine and 2-PAM showed increases in the soman LD50 of at least 40-fold compared to the untreated control group and at least 25-fold compared to the atropine/2-PAM group. The two dose levels of pyridostigmine bromide showed similar effectiveness.

Additional studies in rhesus monkeys and guinea pigs also showed effectiveness of pyridostigmine bromide (in the presence of post-soman administration of atropine and 2-PAM). The magnitude of effect in guinea pigs was smaller than that in monkeys (soman LD50 increased 4- to 7-fold compared to untreated control and 2- to 4-fold compared to atropine/ 2-PAM alone).

Pyridostigmine bromide produced only small and inconsistent effects in studies in rats, mice, and rabbits. It is thought that the effect of pyridostigmine bromide in rats and mice is masked by high blood levels of the enzyme carboxylesterase, which eliminates soman from blood and makes those species highly resistant to soman. In a study in which rats were given an inhibitor of carboxylesterase, pretreatment with pyridostigmine bromide plus atropine and 2-PAM increased the LD50 of soman 8.5-fold compared to untreated controls. Humans have little or no carboxylesterase in blood.

Animal studies have shown that pyridostigmine bromide pretreatment was effective only when animals were given atropine and 2-PAM after exposure to soman.

16 HOW SUPPLIED/STORAGE AND HANDLING

16.1 How Supplied

Pyridostigmine bromide tablets, USP, 30 mg, are round, white tablets imprinted with the letters "PBT."

Immediate Container: Individually sealed blister or strip package containing twenty-one (21) tablets which is supplied in a protective sleeve.

NDC 72458-128-03

Secondary Container: A protective foil overwrap containing ten (10) immediate containers (sleaved blister of strip packages) containing 210 tablets total.

NDC 72458-128-04

NSN 6505-01-178-7903. The NSN refers to the secondary container unit that is ordered from supply (1 of this stock number is one foil overwrap of 10 blister packs).

Shipping Carton Contents: Ten (10) foil overwrap packages containing ten (10) blister or strip packages containing 2,100 tablets total.

16.2 Storage and Handling

Store refrigerated between 2°C to 8°C (36°F to 46°F) in carton or foil overwrap to protect from light until the expiration date. Once removed from refrigerator, store at 20°C to 25°C (68°F to 77°F) [see USP controlled room temperature] in carton or foil overwrap for up to 5 years minus half of the time spent under refrigerated storage or until the expiration date, whichever comes first. Following removal of the blister packages from the foil overwrap, discard the contents of the blister package after 14 months or after the expiration date, whichever comes first.

17 PATIENT COUNSELING INFORMATION

Advise personnel to read the FDA-approved patient labeling (Patient Information).

Indication and Conditions of Use

Advise personnel of the following:

- Pyridostigmine bromide is approved as a pretreatment against the lethal effects of the chemical nerve agent soman (GD). Pyridostigmine bromide has not been approved for use against other chemical nerve agents including Sarin (GB), Tabun (GA), and VX [see Indications and Usage (1)].
  The approval is based on safety studies in humans and effectiveness studies conducted in animals. It is not ethical to study the efficacy in humans. Human studies would require exposing people to the deadly effects of nerve agents, risking poisoning them or even killing them. Studies in monkeys and guinea pigs show that pretreatment with pyridostigmine bromide makes the antidotes (atropine and 2-PAM) work better against soman (GD) [see Clinical Studies (14)].
- The main protection against chemical weapons is the chemical protective mask and battle dress overgarments [see Dosage and Administration (2.1, 2.2) and Warnings and Precautions (5.1)].
- Pyridostigmine bromide is used as a pretreatment against a soman nerve agent attack. Based on the animal studies, it is thought that any potential benefits from use of pyridostigmine bromide occur only if:
  (1) It is taken at least several hours before, but not right before, exposure to the nerve agent soman. If it is taken right before (when the nerve gas attack alarm is given) or during nerve agent exposure, it may not work and may make the effects of soman worse.
  (2) Atropine and 2-PAM are used when symptoms of nerve agent poisoning occur [see Dosage and Administration (2.1, 2.2)].

Dosage and Administration [see Dosage and Administration (2.1, 2.2)]

Inform personnel of the following:

- The chain of command will instruct when it is time to take pyridostigmine bromide, based on the threat of exposure to soman nerve agents.
- Take one tablet orally every 8 hours until the chain of command instructs to stop taking pyridostigmine bromide.
- Take pyridostigmine bromide tablets only as prescribed.
- If a dose is missed, take the missed dose as soon as possible. Do not take double or extra doses.
- There is no known advantage to taking extra pyridostigmine bromide right before soman exposure.
- Discontinue pyridostigmine bromide after nerve agent exposure has occurred, instead:
  - Persons experiencing most or all of the MILD symptoms of nerve agent poisoning (runny nose; watery eyes; small, pinpoint pupils; eye pain; blurred vision; drooling and excessive sweating; cough; chest tightness; rapid breathing; diarrhea; increased urination; confusion; drowsiness; weakness; headache; nausea, vomiting, and/ or abdominal pain; slow or fast heart rate; and/or abnormally low or high blood pressure) should IMMEDIATELY AVOID INHALATION (hold their breath) AND PUT ON THEIR PROTECTIVE MASK.
  - Then atropine and 2-PAM must be administered.
- Contact their unit medical officer if adverse reactions from pyridostigmine bromide continue and limit duty performance.

Risks in Individuals with Certain Conditions [see Contraindications (4), Warnings and Precautions (5.2), and Use in Specific Populations (8.1)]

Instruct personnel to inform their healthcare provider before taking pyridostigmine bromide if they:

- Are pregnant
- Have asthma
- Are allergic to bromide, pyridostigmine, or anticholinesterase drugs
- Take a beta blocker (a medicine to treat, e.g., high blood pressure)
- Have high eye pressure (glaucoma)
- Have any other medical condition, including heart problems, genitourinary or gastrointestinal obstruction, or reflux esophagitis (GERD)

Collection of Information

The Department of Defense (DoD) may collect information on the use of pyridostigmine bromide to help decide how best to protect deployed forces in the future. Information that identifies individual persons will remain confidential. However, the FDA may review any data collected by DoD for the purpose of evaluating pyridostigmine bromide.

Questions and Requests for Information

Questions about personnel rights and welfare should be directed to the unit medical officer or e-mailed to usarmy.detrick.medcom-usamrmc.mbx.regulatory-affairs@health.mil.

Personnel can receive information about pyridostigmine bromide from unit medical officers or medics. Questions about pyridostigmine bromide can also be e-mailed directly to the US Army Medical Research and Development Command at address
usarmy.detrick.medcom-usamrmc.mbx.regulatory-affairs@health.mil. .

Distributed by:
Defense Logistics Agency Troop Support,
Philadelphia Medical Directorate
700 Robbins Ave
Philadelphia, PA 19111

For:
Defense Health Agency
Research & Development - Medical Research and Development Command
ATTN: FCMR-ORA
1541 Porter Street
Fort Detrick, MD 21702-9247

PRINCIPAL DISPLAY PANEL - 21 Tablet Blister Pack

00000000X

NDC 72458-128-03

Rx Only
Quantity: 21 Tablets

NSN 6505-01-178-7903
PYRIDOSTIGMINE BROMIDE TABLETS USP, 30 MG
[Soman Nerve Agent Pretreatment Pyridostgimine (SNAPP)]

Date removed from the overwrap ____ /____ /____
Discard contents 14 months after removal from the
overwrap or after expiration date, whichever comes first.

Stop Taking Pyridostigmine Tablets:

- If You Are Exposed to Soman Nerve Agent
- If You Hear a Gas Attack Alarm

When stored refrigerated (2°C to 8°C)(36°F to 46°F)

Manufactured by
Bausch Health
Companies Inc.,
Laval, Quebec
H7L 4A8 for
US Department
of Defense

LOT: 0000000
EXP: YYYY/MM

PRINCIPAL DISPLAY PANEL - 2100 Tablet Blister Pack Bag Label

NSN 6505-01-178-7903

PYRIDOSTIGMINE BROMIDE TABLETS, USP, 30 mg
(Soman Nerve Agent Pretreatment Pyridostigmine Bromide (SNAPP))

Each Tablet Contains 30 mg of Pyridostigmine Bromide

Unit of Issue: 1 0 Packages of 1 0 Blister Packs Each
Quantity: 2100 Tablets

Rx only
Lot No.: LLLLLL
Expiration Date:YYYY/MM

Store refrigerated (2°C to 8°C) (36°F to 46°F) in carton or foil overwrap to protect
from light until the expiration date.

Once removed from refrigerator, store at controlled room temperature
(20°C to 25°C) (68°F to 77°F) in carton or foil overwrap for up to 5 years minus
half of the time spent under refrigerated storage or the expiration date,
whichever comes first.

Date removed from refrigerator ____ /____ /____

Manufactured by Bausch Health Companies Inc., Laval, Quebec H7L 4A8 for US Department of Defense

draft_SHL_FRG_24_09-11

PRINCIPAL DISPLAY PANEL - 21 Tablet Blister Pack Label

NSN 6505-01-178-7903
PYRIDOSTIGMINE BROMIDE TABLETS, USP, 30 mg
(Soman Nerve Agent Pretreatment Pyridostigmine (SNAPP)) Each Tablet contains 30 mg
Quantity: 1 Blister Pack of 21 Tablets
Lot: LLLLLLL
Exp Date: YYYY/MM
When stored refrigerated (2°C to 8°C) (36°F to 46°F)
Discard contents 14 months after removal from the overwrap or after expiration date, whichever comes first.
Manufactured by Bausch Health Companies Inc., Laval, Quebec H7L 4A8 for US Department of Defense
NSN 6505-01-178-7903
PYRIDOSTIGMINE BROMIDE TABLETS, USP, 30 mg
(Soman Nerve Agent Pretreatment Pyridostigmine (SNAPP)) Each Tablet contains 30 mg
Quantity: 1 Blister Pack of 21 Tablets
Lot: LLLLLLL
Exp Date: YYYY/MM
When stored refrigerated (2°C to 8°C) (36°F to 46°F)
Discard contents 14 months after removal from the overwrap or after expiration date, whichever comes first.
Manufactured by Bausch Health Companies Inc., Laval, Quebec H7L 4A8 for US Department of Defense

PRINCIPAL DISPLAY PANEL - 210 Tablet Blister Pack Package Label

NDC 72458-128-04
Rx Only

NSN 6505-01-178-7903
PYRIDOSTIGMINE BROMIDE
TABLETS, USP, 30 MG
[Soman Nerve Agent Pretreatment
Pyridostigmine (SNAPP)]

Unit of Issue: 1 Package of 10 Blister Packs
Quantity: 210 Tablets

Store refrigerated (2°C to 8°C) (36°F to 46°F), in foil
overwrap to protect from light, until the expiration date.

Once removed from refrigerator store at controlled room
temperature (20°C to 25°C) (68°F to 77°F) in foil overwrap for
up to 5 years minus half of the time spent under refrigerated
storage or until the expiration date, whichever comes first.
Following removal of the blister packages from the foil
overwrap, discard the contents of each blister package after
14 months or the expiration date, whichever comes first.

Date removed from refrigerator _____/_____/_____

Manufactured by Bausch Health Companies Inc.,
Laval, Quebec H7L 4A8 for US Department of Defense

LOT: 0000000
EXP: YYYY/MM

00000000X